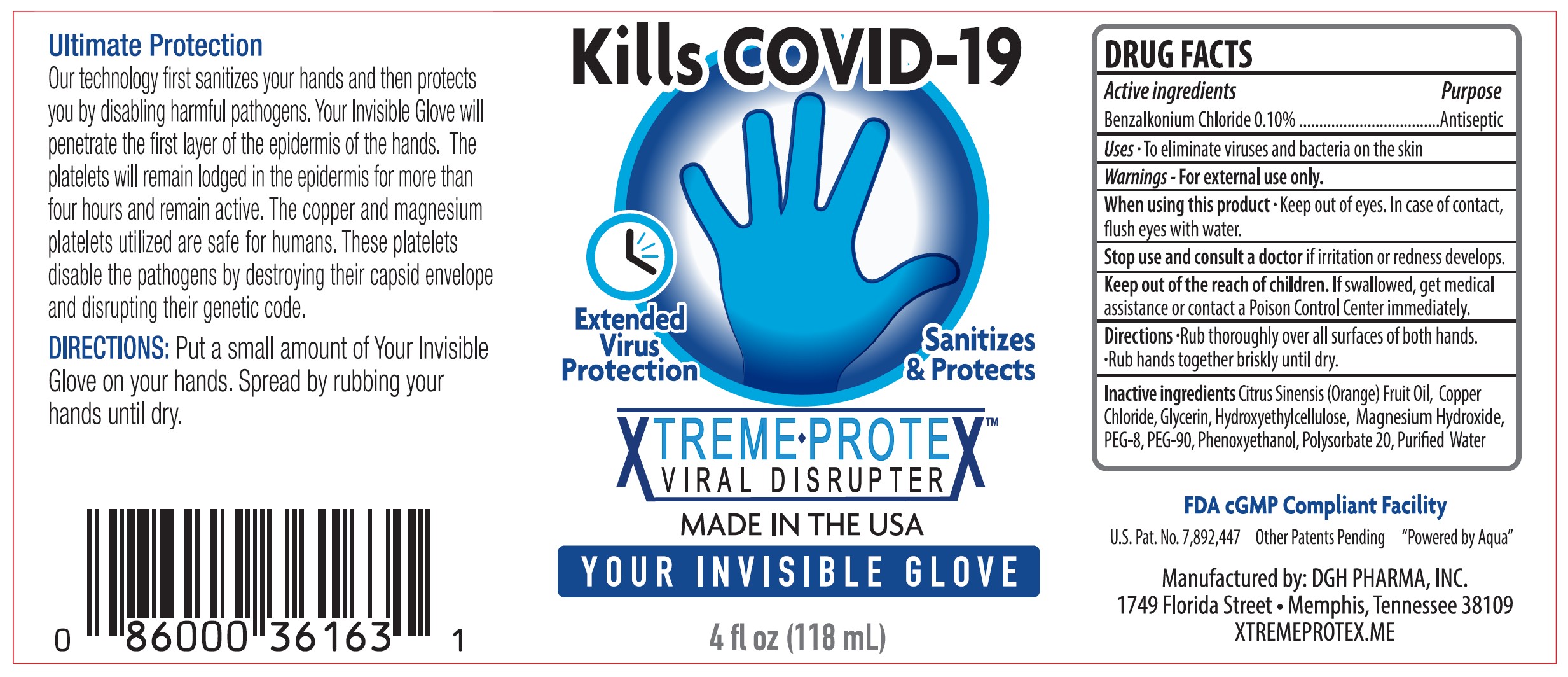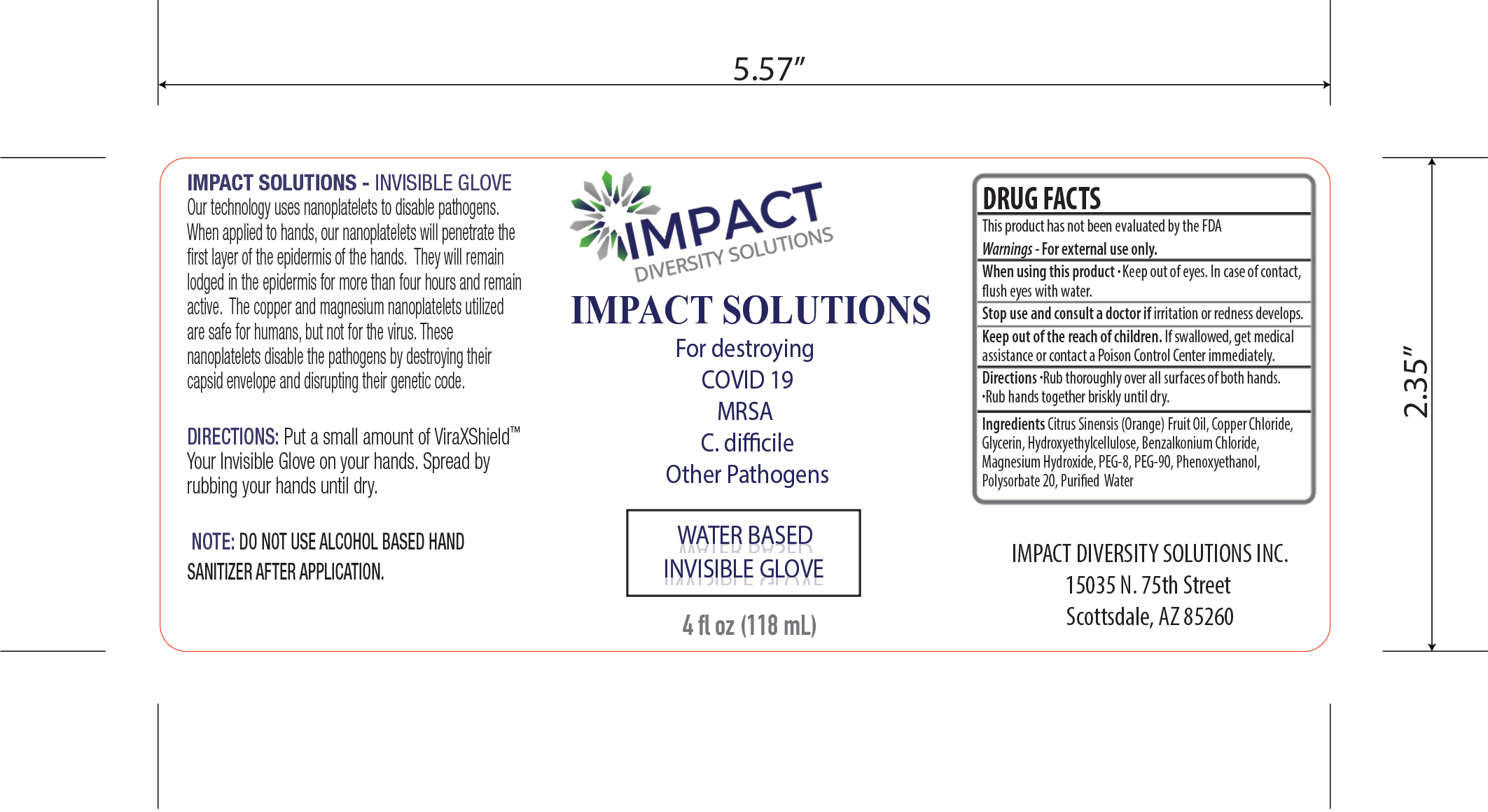 DRUG LABEL: Hand Sanitizer
NDC: 77238-231 | Form: GEL
Manufacturer: DGH Pharma, Inc.
Category: otc | Type: HUMAN OTC DRUG LABEL
Date: 20220729

ACTIVE INGREDIENTS: BENZALKONIUM CHLORIDE 0.1 g/100 mL
INACTIVE INGREDIENTS: CUPRIC CHLORIDE 0.201 g/100 mL; MAGNESIUM HYDROXIDE 0.05 g/100 mL; GLYCERIN 1.65 g/100 mL; PHENOXYETHANOL 0.4 g/100 mL; POLYETHYLENE GLYCOL 4000 1.95 g/100 mL; POLYETHYLENE GLYCOL 400 1.65 g/100 mL; WATER; POLYSORBATE 20 2 g/100 mL; HYDROXYETHYL CELLULOSE, UNSPECIFIED 0.65 g/100 mL; LIMONENE, (+)- 0.18 g/100 mL

Hand Sanitizer Cu - 32015

Active Ingredient(s)

Benzalkonium Chloride 0.10% w/w. Purpose: Antiseptic

Purpose

Antiseptic, Hand Sanitizer

Use

To eliminate viruses and bacteria on the skin

Warnings

For external use only.

When using this product keep out of eyes. In case of contact, flush eyes with water.
Stop use and ask a doctor if irritation or redness develops
Keep out of reach of children. If swallowed, get medical assistance or contact a Poison Control Center immediately.

Stop use and ask a doctor if irritation or redness develops.

Keep out of reach of children. If swallowed, get medical assistance or contact a Poison Control Center immediately.

Directions

- Rub thoroughly over all surfaces of both hands.
- Rub hands toghether briskly unitl dry.

Inactive ingredients

Citrus Sinensis (Orange) Fruit Oil, Copper Chloride, Glycerin, Hydroxyethylcellulose, Magnesium Hydroxide, PEG-8, PEG-90, Phenoxyethanol, Polysorbate 20, Purified Water